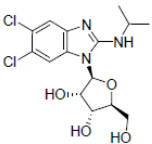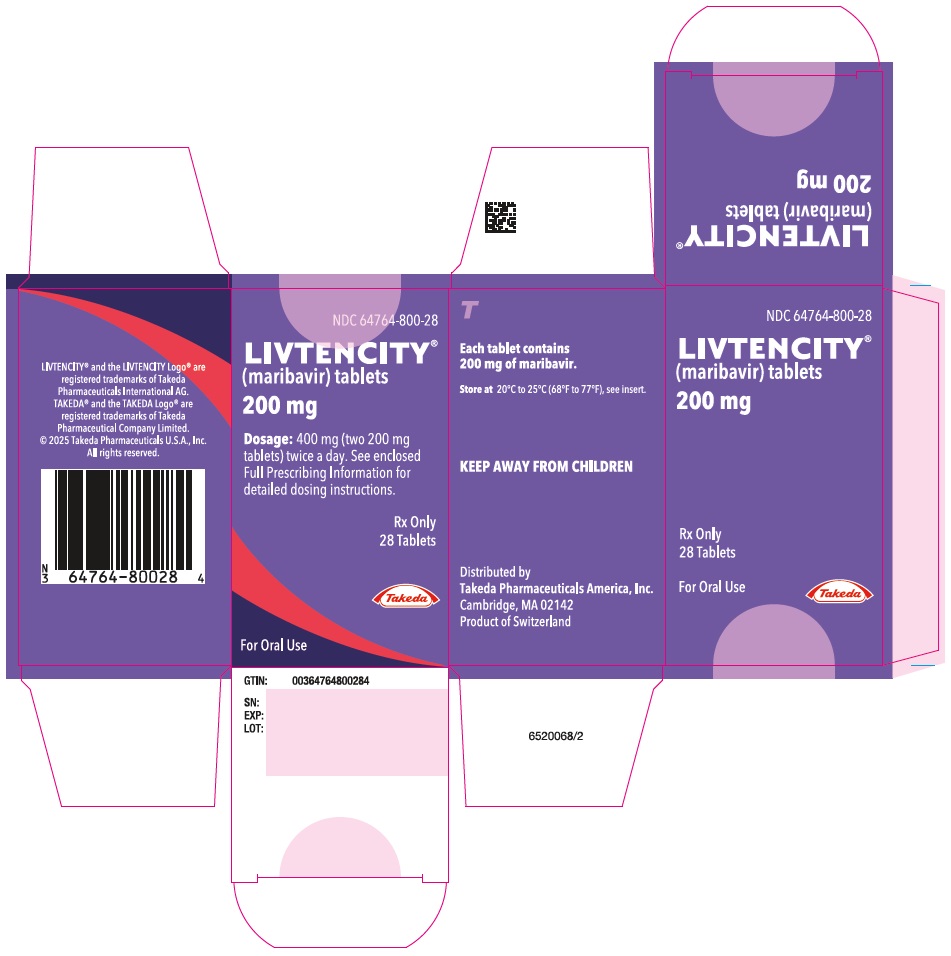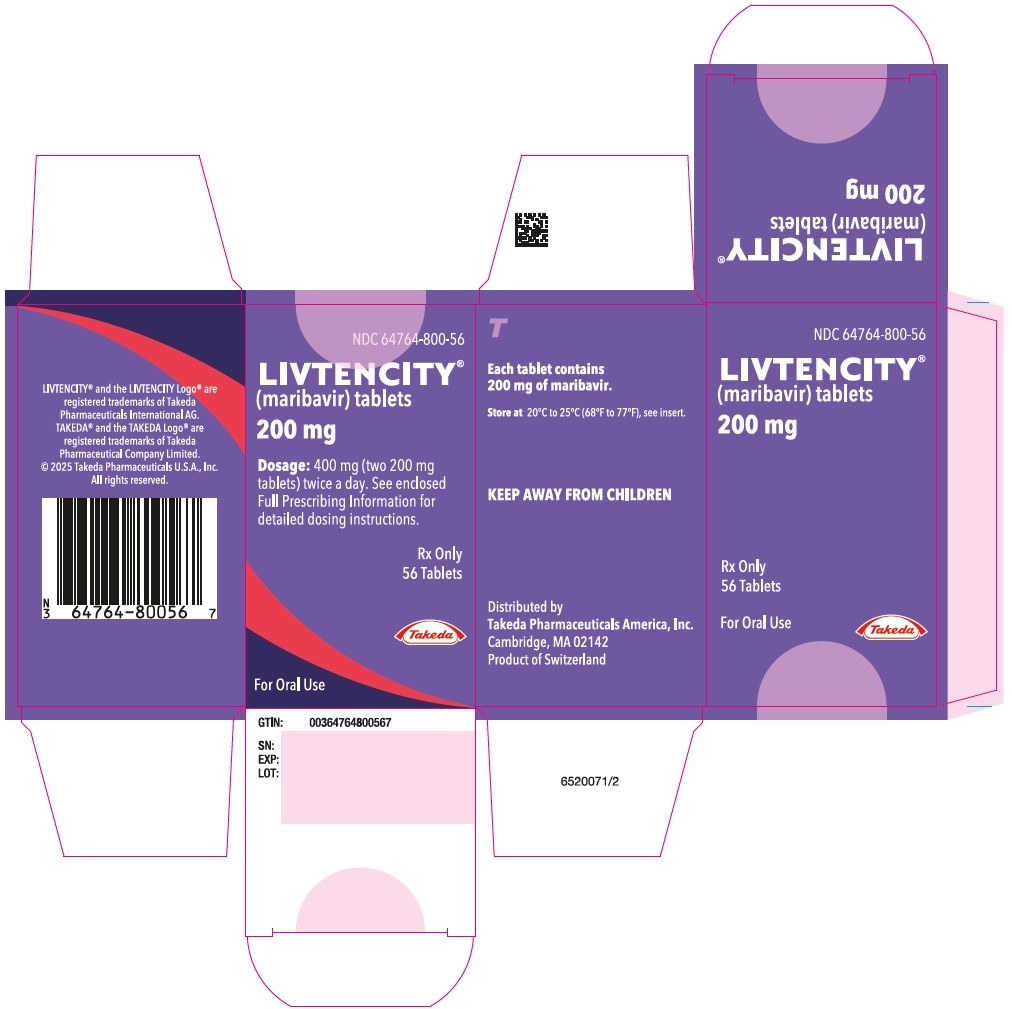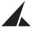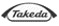 DRUG LABEL: Livtencity
NDC: 64764-800 | Form: TABLET, COATED
Manufacturer: Takeda Pharmaceuticals America, Inc.
Category: prescription | Type: HUMAN PRESCRIPTION DRUG LABEL
Date: 20260127

ACTIVE INGREDIENTS: MARIBAVIR 200 mg/1 1
INACTIVE INGREDIENTS: Microcrystalline cellulose; SODIUM STARCH GLYCOLATE TYPE A; Magnesium stearate; POLYVINYL ALCOHOL, UNSPECIFIED; Titanium dioxide; POLYETHYLENE GLYCOL, UNSPECIFIED; Talc; FD&C Blue NO. 1

HIGHLIGHTS OF PRESCRIBING INFORMATION

These highlights do not include all the information needed to use LIVTENCITY safely and effectively. See full prescribing information for LIVTENCITY.
LIVTENCITY® (maribavir) tablets, for oral use
Initial U.S. Approval: 2021

RECENT MAJOR CHANGES

Dosage and Administration, (2.2, 2.3, 2.4) | 11/2025
Warnings and Precautions,
Risk of Adverse Reactions or Loss of Virologic Response
Due to Drug Interactions (5.3) | 11/2025

1 INDICATIONS AND USAGE

LIVTENCITY is a cytomegalovirus (CMV) pUL97 kinase inhibitor indicated for the treatment of adults and pediatric patients (12 years of age and older and weighing at least 35 kg) with post-transplant CMV infection/disease that is refractory to treatment (with or without genotypic resistance) with ganciclovir, valganciclovir, cidofovir or foscarnet. (1, 8.4)

2 DOSAGE AND ADMINISTRATION

400 mg (two 200 mg tablets) orally twice daily with or without food. (2.1, 8.4)

3 DOSAGE FORMS AND STRENGTHS

Tablets: 200 mg of maribavir. (3)

4 CONTRAINDICATIONS

None. (4)

5 WARNINGS AND PRECAUTIONS

- LIVTENCITY may antagonize the antiviral activity of ganciclovir and valganciclovir. Coadministration is not recommended. (5.1, 7.1)
- Virologic failure can occur during and after treatment with LIVTENCITY. Monitor CMV DNA levels and check for resistance if patient does not respond to treatment. Some maribavir pUL97 resistance-associated substitutions confer cross-resistance to ganciclovir and valganciclovir. (5.2, 12.4, 14.1)
- The concomitant use of LIVTENCITY and certain drugs may result in potentially significant drug interactions, some of which may lead to reduced therapeutic effect of LIVTENCITY or adverse reactions of concomitant drugs. (5.1, 5.3, 7.1, 7.2, 7.3)
- LIVTENCITY has the potential to increase the drug concentrations of certain immunosuppressant drugs where minimal concentration changes may lead to serious adverse events (including tacrolimus, cyclosporine, sirolimus and everolimus). Frequently monitor immunosuppressant drug levels throughout treatment with LIVTENCITY, especially following initiation and after discontinuation of LIVTENCITY and adjust the dose, as needed. (5.3)

6 ADVERSE REACTIONS

The most common adverse events (all grades, >10%) in subjects treated with LIVTENCITY were taste disturbance, nausea, diarrhea, vomiting, and fatigue. (6.1)

To report SUSPECTED ADVERSE REACTIONS, contact Takeda Pharmaceuticals America, Inc. at 1-877-TAKEDA-7 (1-877-825-3327) or FDA at 1-800-FDA-1088 or www.fda.gov/medwatch.

7 DRUG INTERACTIONS

- Refer to the full prescribing information for important drug interactions with LIVTENCITY. (5.1, 5.3, 7)
- Coadministration with strong CYP3A4 inducers is not recommended, except with a dose adjustment when coadministered with selected anticonvulsants (carbamazepine and phenytoin). When coadministered with the moderate CYP3A4 inducers rifabutin (antimycobacterial) or phenobarbital (anticonvulsant), a dose adjustment is recommended. (2.2, 2.3, 7.3)

FULL PRESCRIBING INFORMATION

1 INDICATIONS AND USAGE

LIVTENCITY® is indicated for the treatment of adults and pediatric patients (12 years of age and older and weighing at least 35 kg) with post-transplant cytomegalovirus (CMV) infection/disease that is refractory to treatment (with or without genotypic resistance) with ganciclovir, valganciclovir, cidofovir or foscarnet [see Use in Specific Populations (8.4) and Clinical Studies (14)].

2 DOSAGE AND ADMINISTRATION

2.1 Recommended Dosage

The recommended dosage in adults and pediatric patients (12 years of age and older and weighing at least 35 kg) is 400 mg (two 200 mg tablets) taken orally twice daily with or without food [see Use in Specific Populations (8.4), Clinical Pharmacology (12.3) and Clinical Studies (14)].

2.2 Dosage Adjustment When Coadministered with Anticonvulsants

If LIVTENCITY is coadministered with carbamazepine, increase the dosage of LIVTENCITY to 800 mg (four 200 mg tablets) twice daily [see Drug Interactions (7.3) and Clinical Pharmacology (12.3)].

If LIVTENCITY is coadministered with phenytoin or phenobarbital, increase the dosage of LIVTENCITY to 1,200 mg (six 200 mg tablets) twice daily [see Drug Interactions (7.3) and Clinical Pharmacology (12.3)].

2.3 Dosage Adjustment When Coadministered with Rifabutin

If LIVTENCITY is co-administered with rifabutin, increase the dosage of LIVTENCITY to 800 mg (four 200 mg tablets) twice daily [see Drug Interactions (7.3) and Clinical Pharmacology (12.3)].

2.4 Administration Instructions

The immediate-release tablets can be taken as whole, dispersed or crushed tablets by mouth, or as dispersed tablets through a nasogastric or orogastric tube (French size 10 or larger). The suspension may be prepared ahead of time and stored at room temperature for up to 8 hours.

Administration of Dispersed Tablets or Crushed Tablets by Mouth

1. Place the appropriate number of tablets for the prescribed dose into a suitable container. If desired, the tablets may be crushed. Add the appropriate volume of drinking water (other liquids have not been tested) to make a suspension (see Table 1 below).
  Table 1: Number of Tablets and Volume of Drinking Water Needed to Make a Suspension for Administration of Dispersed or Crushed Tablets by Mouth
  Recommended Dosage | Number of 200 mg Tablets | Volume of Drinking Water
  400 mg | Two | 30 mL
  800 mg | Four | 60 mL
  1,200 mg | Six | 90 mL
2. Swirl the container gently to keep the particles from settling, and administer the suspension before it settles. The mixture will have a bitter taste.
3. Rinse the container with 15 mL of drinking water and administer the rinse water.
4. Repeat Step 3. Visually confirm that no particles are left in the container. If particles remain, repeat Step 3.

Administration of Dispersed Tablets through a Nasogastric (NG) or Orogastric (OG) Tube

1. Remove the cap (if applicable) and plunger out of a 50 or 60 mL catheter-tip compatible syringe or equivalent. Add two tablets into the syringe body and place the plunger back in the syringe. Only two tablets can be administered via NG or OG tube at a time.
2. Draw 30 mL of drinking water (other liquids have not been tested) into the syringe and hold the syringe with the tip pointing upward. Pull the plunger further to a higher volume position to have some air space in the syringe. Place the cap back on the syringe (if applicable). Shake the syringe well (careful not to spill the contents) for about 30 to 45 seconds or until the tablets are completely dispersed.
3. Once the tablets are completely dispersed in the syringe, remove the cap from the syringe again (if applicable) and attach the syringe to the NG or OG tube and administer the dispersion before it settles.
4. Draw 15 mL of water using the same syringe and flush through the same NG or OG tube.
5. Repeat Step 4 and make sure no particles are left in the syringe by visual inspection. If particles remain, repeat Step 4.
6. For doses of 800 mg (four 200 mg tablets) and 1,200 mg (six 200 mg tablets) [see Dosage and Administration (2.2, 2.3)], repeat Steps 1-5 until prescribed dose is reached. The same syringe, NG or OG tube can be used.

3 DOSAGE FORMS AND STRENGTHS

Tablet: 200 mg, blue, oval shaped convex tablet debossed with "SHP" on one side and "620" on the other side.

4 CONTRAINDICATIONS

None.

5 WARNINGS AND PRECAUTIONS

5.1 Risk of Reduced Antiviral Activity When Coadministered with Ganciclovir and Valganciclovir

LIVTENCITY may antagonize the antiviral activity of ganciclovir and valganciclovir by inhibiting human CMV pUL97 kinase, which is required for activation/phosphorylation of ganciclovir and valganciclovir. Coadministration of LIVTENCITY with ganciclovir or valganciclovir is not recommended [see Drug Interactions (7.1) and Microbiology (12.4)].

5.2 Virologic Failure During Treatment and Relapse Post-Treatment

Virologic failure due to resistance can occur during and after treatment with LIVTENCITY. Virologic relapse during the post-treatment period usually occurred within 4-8 weeks after treatment discontinuation. Some maribavir pUL97 resistance-associated substitutions confer cross-resistance to ganciclovir and valganciclovir. Monitor CMV DNA levels and check for maribavir resistance if the patient is not responding to treatment or relapses [see Microbiology (12.4) and Clinical Studies (14.1)].

5.3 Risk of Adverse Reactions or Loss of Virologic Response Due to Drug Interactions

The concomitant use of LIVTENCITY and certain drugs may result in potentially significant drug interactions, some of which may lead to reduced therapeutic effect of LIVTENCITY or adverse reactions of concomitant drugs [see Drug Interactions (7)].

See Table 4 for steps to prevent or manage these possible or known significant drug interactions, including dosing recommendations. Consider the potential for drug interactions prior to and during LIVTENCITY therapy; review concomitant medications during LIVTENCITY therapy and monitor for adverse reactions.

Maribavir is primarily metabolized by CYP3A4. Drugs that are strong inducers of CYP3A4 are expected to decrease maribavir plasma concentrations and may result in reduced virologic response. Thus, coadministration of LIVTENCITY with these drugs is not recommended, except with a dose adjustment when coadministered with selected anticonvulsants (carbamazepine and phenytoin). With moderate CYP3A4 inducers rifabutin (antimycobacterial) and phenobarbital (anticonvulsant), a dose adjustment is recommended [see Dosage and Administration (2.2, 2.3) and Drug Interactions (7.3)]. For other moderate CYP3A4 inducers, the appropriate maribavir dose adjustment has not been determined.

Use with Immunosuppressant Drugs

LIVTENCITY has the potential to increase the drug concentrations of certain immunosuppressant drugs where minimal concentration changes may lead to serious adverse events (including tacrolimus, cyclosporine, sirolimus and everolimus). Frequently monitor immunosuppressant drug levels throughout treatment with LIVTENCITY, especially following initiation and after discontinuation of LIVTENCITY and adjust the immunosuppressant dose, as needed [see Drug Interactions (7.3) and Clinical Pharmacology (12.3)].

6 ADVERSE REACTIONS

6.1 Clinical Trials Experience

Because clinical trials are conducted under widely varying conditions, adverse reaction rates observed in the clinical trials of a drug cannot be directly compared to rates in the clinical trials of another drug and may not reflect the rates observed in practice.

The safety of LIVTENCITY was evaluated in one Phase 3 multicenter, randomized, open-label, active-control trial in which 352 adult transplant recipients were randomized, and treated with LIVTENCITY (N=234) or Investigator-Assigned Treatment (IAT) consisting of monotherapy or dual therapy with ganciclovir, valganciclovir, foscarnet, or cidofovir as dosed by the investigator (N=116) for up to 8-weeks following a diagnosis of CMV infection/disease refractory to treatment (with or without genotypic resistance) with ganciclovir, valganciclovir, foscarnet or cidofovir. The mean treatment durations (SD) for LIVTENCITY and IAT were 48.6 (± 13.82) and 31.2 (± 16.91) days, respectively. The most common adverse events occurring in more than 10% of subjects receiving LIVTENCITY are outlined in Table 2.

Table 2: Adverse Events (All Grades) Reported in >10% of Subjects in the LIVTENCITY Group in Trial 303
ADVERSE EVENT | LIVTENCITY N=234 (%) | IAT [IAT (Investigator-Assigned Treatment) included monotherapy or dual therapy with ganciclovir, valganciclovir, foscarnet, or cidofovir as dosed by the investigator.] N=116 (%)
Taste disturbance [taste disturbance includes the following reported preferred terms: ageusia, dysgeusia, hypogeusia and taste disorder.] | 46 | 4
Nausea | 21 | 22
Diarrhea | 19 | 21
Vomiting | 14 | 16
Fatigue | 12 | 9

Similar proportions of subjects experienced serious adverse events (38% in the LIVTENCITY group and 37% in the IAT group). The most common serious adverse event in both treatment groups occurred in the Infections and Infestations System Organ Class (SOC) (23% in the LIVTENCITY group and 15% in the IAT group) with CMV infection and disease being the most common in both groups.

A higher proportion of subjects in the IAT group discontinued study medication due to an adverse event compared to the LIVTENCITY group (32% in the IAT group vs 13% in the LIVTENCITY group). The most commonly reported causes that led to study drug discontinuation were neutropenia (9%) and acute kidney injury (5%) in the IAT group and dysgeusia, diarrhea, nausea, and recurrence of underlying disease (each reported at 1%) in the LIVTENCITY group.

Taste disturbance occurred in 46% of subjects treated with LIVTENCITY. These events rarely led to discontinuation of LIVTENCITY (1%) and, for 37% of the subjects, these events resolved while on therapy (median duration 43 days; range 7 to 59 days). For the subjects with ongoing taste disturbance after drug discontinuation, resolution occurred in 89%. In subjects with resolution of symptoms after drug discontinuation, the median duration of symptoms off treatment was 6 days (range 2 to 85 days).

Laboratory Abnormalities

Selected laboratory abnormalities reported in subjects with refractory (with or without genotypic resistance) CMV infections in Trial 303 are presented in Table 3.

Table 3: Selected Laboratory Abnormalities Reported in Trial 303
Laboratory Parameter | LIVTENCITY N=234 n (%) | IAT N=116 n (%)
Neutrophils (cells/µL)
<500 | 4 (2) | 4 (3)
≥500 to <750 | 7 (3) | 7 (6)
≥750 to <1,000 | 10 (4) | 6 (5)
Hemoglobin (g/dL)
<6.5 | 3 (1) | 1 (1)
≥6.5 to <8.0 | 34 (15) | 23 (20)
≥8.0 to <9.5 | 76 (32) | 33 (28)
Platelets (cells/µL)
<25,000 | 11 (5) | 6 (5)
≥25,000 to <50,000 | 27 (12) | 10 (9)
≥50,000 to <100,000 | 41 (18) | 20 (17)
Creatinine (mg/dL)
>2.5 | 16 (7) | 12 (10)
>1.5 to ≤2.5 | 78 (33) | 29 (25)

7 DRUG INTERACTIONS

7.1 Reduced Antiviral Activity When Coadministered with Ganciclovir or Valganciclovir

LIVTENCITY is not recommended to be coadministered with valganciclovir/ganciclovir (vGCV/GCV). LIVTENCITY may antagonize the antiviral activity of ganciclovir and valganciclovir by inhibiting human CMV pUL97 kinase, which is required for activation/phosphorylation of ganciclovir and valganciclovir [see Warnings and Precautions (5.1) and Microbiology (12.4)].

7.2 Potential for Other Drugs to Affect LIVTENCITY

Maribavir is a substrate of CYP3A4. Coadministration of LIVTENCITY with strong inducers of CYP3A4 is not recommended, except with a dose adjustment when coadministered with selected anticonvulsants (carbamazepine and phenytoin). With the moderate CYP3A4 inducers, rifabutin (antimycobacterial) and phenobarbital (anticonvulsant), a dose adjustment is recommended [see Dosage and Administration (2.2, 2.3) and Drug Interactions (7.3)]. For other moderate CYP3A4 inducers, the appropriate maribavir dose adjustment has not been determined.

7.3 Potential for LIVTENCITY to Affect Other Drugs

Maribavir is an inhibitor of P-gp and breast cancer resistance protein (BCRP). Coadministration of LIVTENCITY with drugs that are substrates of P-gp and/or BCRP where minimal concentration changes may lead to serious adverse events may result in a clinically relevant increase in plasma concentrations of these substrates (see Table 4). Table 4 provides a list of established or potentially clinically significant drug interactions, based on either clinical drug interaction studies or predicted interactions due to the expected magnitude of interaction and potential for serious adverse events or decrease in efficacy [see Warnings and Precautions (5.3) and Clinical Pharmacology (12.3)].

Table 4: Established and Other Potentially Significant Drug Interactions [This table is not all inclusive.]
Concomitant Drug Class: Drug Name | Effect on Concentration | Clinical Comments
Antiarrhythmics
Digoxin [The interaction between LIVTENCITY and the concomitant drug was evaluated in a clinical study [see Clinical Pharmacology (12.3)].] | ↑ Digoxin | Use caution when LIVTENCITY and digoxin are coadministered. Monitor serum digoxin concentrations. The dose of digoxin may need to be reduced when coadministered with LIVTENCITY. [Refer to the respective prescribing information.]
Anticonvulsants
Carbamazepine | ↓ Maribavir | A dose adjustment of LIVTENCITY to 800 mg twice daily is recommended when coadministered with carbamazepine.
Phenobarbital | ↓ Maribavir | A dose adjustment of LIVTENCITY to 1,200 mg twice daily is recommended when coadministration with phenobarbital.
Phenytoin | ↓ Maribavir | A dose adjustment of LIVTENCITY to 1,200 mg twice daily is recommended when coadministration with phenytoin.
Antimycobacterials
Rifabutin | ↓ Maribavir | A dose adjustment of LIVTENCITY to 800 mg twice daily is recommended when coadministered with rifabutin.
Rifampin | ↓ Maribavir | Coadministration of LIVTENCITY and rifampin is not recommended due to potential for a decrease in efficacy of LIVTENCITY.
Herbal Products
St. John's wort | ↓ Maribavir | Coadministration of LIVTENCITY and St. John's wort is not recommended due to potential for a decrease in efficacy of LIVTENCITY.
HMG-CoA Reductase Inhibitors
Rosuvastatin | ↑ Rosuvastatin | The patient should be closely monitored for rosuvastatin-related events, especially the occurrence of myopathy and rhabdomyolysis.
Immunosuppressants
Cyclosporine | ↑ Cyclosporine | Frequently monitor cyclosporine levels throughout treatment with LIVTENCITY, especially following initiation and after discontinuation of LIVTENCITY and adjust dose, as needed.
Everolimus | ↑ Everolimus | Frequently monitor everolimus levels throughout treatment with LIVTENCITY, especially following initiation and after discontinuation of LIVTENCITY and adjust dose, as needed.
Sirolimus | ↑ Sirolimus | Frequently monitor sirolimus levels throughout treatment with LIVTENCITY, especially following initiation and after discontinuation of LIVTENCITY and adjust dose, as needed.
Tacrolimus | ↑ Tacrolimus | Frequently monitor tacrolimus levels throughout treatment with LIVTENCITY, especially following initiation and after discontinuation of LIVTENCITY and adjust dose, as needed.
↓=decrease, ↑=increase.

7.4 Drugs without Clinically Significant Interactions with LIVTENCITY

No clinically significant interactions were observed in clinical drug-drug interaction studies of LIVTENCITY and ketoconazole, antacid, caffeine, warfarin, voriconazole, dextromethorphan, or midazolam [see Clinical Pharmacology (12.3)].

8 USE IN SPECIFIC POPULATIONS

8.1 Pregnancy

Risk Summary

No adequate human data are available to establish whether LIVTENCITY poses a risk to pregnancy outcomes. In animal reproduction studies, embryo-fetal survival was decreased in rats, but not in rabbits, at maribavir exposures less than those observed in humans at the recommended human dose (RHD) (see Data).

The background risk of major birth defects and miscarriage for the indicated population is unknown. In the U.S. general population, the estimated background risk of major birth defects and miscarriage in clinically recognized pregnancies is 2-4% and 15-20%, respectively.

Data

Animal Data

In a combined fertility and embryofetal development study, maribavir was administered to male and female rats at oral doses of 100, 200, or 400 mg/kg/day. Females were dosed for 15 consecutive days prior to pairing, throughout pairing, and up to gestation day (GD) 17, while males were dosed 29 days prior to mating and throughout mating. A decrease in the number of viable fetuses and increase in early resorptions and post-implantation losses were observed at ≥100 mg/kg/day (at exposures approximately half the human exposure at the RHD). Intermittent reduced body weight gain was observed in pregnant animals at ≥200 mg/kg/day. Maribavir had no effect on embryo-fetal growth or development at dose levels up to 400 mg/kg/day, at exposures similar to those observed in humans at the RHD.

No significant toxicological effects on embryo-fetal growth or development were observed in rabbits when maribavir was administered at oral doses up to 100 mg/kg/day from GD 8 to 20, at exposures approximately half the human exposure at the RHD.

In the pre-and post-natal developmental toxicity study, maribavir was administered to pregnant rats at oral doses of 50, 150, or 400 mg/kg/day from GD 7 to post-natal day (PND) 21. A delay in developmental milestones was observed, including pinna detachment at doses ≥150 mg/kg/day and eye opening and preputial separation associated with reduced bodyweight gain of the offspring at 400 mg/kg/day. In addition, decreased fetal survival and litter loss was observed due to maternal toxicity and poor maternal care, respectively, at doses ≥150 mg/kg/day. No effects were observed at 50 mg/kg/day (which is estimated to be less than the human exposure at the RHD). No effects on number of offspring, proportion of males, number of live pups, or survival to PND 4 were observed at any dose in the offspring born to the second generation.

8.2 Lactation

Risk Summary

It is not known whether maribavir or its metabolites are present in human or animal milk, affect milk production, or have effects on the breastfed infant. The developmental and health benefits of breastfeeding should be considered along with the mother's clinical need for LIVTENCITY and any potential adverse effects to the breast-fed child.

8.4 Pediatric Use

The recommended dosing regimen in pediatric patients 12 years of age and older and weighing at least 35 kg is the same as that in adults. Use of LIVTENCITY in this age group is based on the following:

- Evidence from controlled studies of LIVTENCITY in adults
- Population pharmacokinetic (PK) modeling and simulation demonstrating that age and body weight had no clinically meaningful effect on plasma exposures of LIVTENCITY
- LIVTENCITY exposure is expected to be similar between adults and children 12 years of age and older and weighing at least 35 kg
- The course of the disease is similar between adults and pediatric patients to allow extrapolation of data in adults to pediatric patients [see Dosage and Administration (2.1), Clinical Pharmacology (12.3) and Clinical Studies (14)]

The safety and effectiveness of LIVTENCITY have not been established in children younger than 12 years of age.

8.5 Geriatric Use

No dosage adjustment is required for patients over 65 years of age based on the results from population pharmacokinetics analysis [see Clinical Pharmacology (12.3)] and efficacy and safety data from the clinical studies. In the clinical Study 303, 54 patients aged 65 years and over were treated with LIVTENCITY. Safety, effectiveness, and pharmacokinetics were consistent between elderly patients (≥65 years) and younger patients (<65 years).

8.6 Impaired Renal Function

No dose adjustment of LIVTENCITY is needed for patients with mild, moderate, or severe renal impairment [see Clinical Pharmacology (12.3)]. Administration of LIVTENCITY in patients with end stage renal disease (ESRD), including patients on dialysis, has not been studied.

8.7 Impaired Hepatic Function

No dose adjustment of LIVTENCITY is needed for patients with mild (Child-Pugh Class A) or moderate (Child-Pugh Class B) hepatic impairment [see Clinical Pharmacology (12.3)]. Administration of LIVTENCITY in patients with severe hepatic impairment has not been studied.

10 OVERDOSAGE

There is no known specific antidote for LIVTENCITY. In case of overdose, it is recommended that the patient be monitored for adverse reactions and appropriate symptomatic treatment instituted. Due to the high plasma protein binding of LIVTENCITY, dialysis is unlikely to reduce plasma concentrations of LIVTENCITY significantly.

11 DESCRIPTION

LIVTENCITY tablets contain maribavir, a benzimidazole riboside CMV pUL97 protein kinase inhibitor. The chemical name of maribavir is 5,6-Dichloro-N-(1-methylethyl)-1-β-L-ribofuranosyl-1H-benzimidazol-2-amine and the structural formula is:

The molecular formula for maribavir is C15H19Cl2N3O4 and its molecular weight is 376.23.

Each 200 mg tablet for oral administration contains 200 mg maribavir and the following inactive ingredients: FD&C Blue #1, magnesium stearate, microcrystalline cellulose, polyethylene glycol, polyvinyl alcohol, sodium starch glycolate, titanium dioxide, and talc.

12 CLINICAL PHARMACOLOGY

12.1 Mechanism of Action

LIVTENCITY is an antiviral drug against human CMV [see Microbiology (12.4)].

12.2 Pharmacodynamics

Exposure-Response

In dose-ranging studies that evaluated doses of 400 mg twice daily and twice daily doses of two and three times the recommended dose, no exposure-response relationship was observed for viral load or probability of unquantifiable plasma CMV DNA.

In Phase 3 Trial 303 that evaluated a maribavir dose of 400 mg twice daily, increasing maribavir exposure was not associated with increased probability of confirmed plasma CMV DNA < LLOQ (lower limit of quantification) at Week 8.

Cardiac Electrophysiology

At three times the recommended dose (approximately twice the peak concentration observed following the recommended dose), LIVTENCITY does not prolong the QT interval to any clinically relevant extent.

12.3 Pharmacokinetics

LIVTENCITY pharmacological activity is due to the parent drug. Following oral administration, plasma maribavir exposure (Cmax and AUC) increased approximately dose-proportionally following a single dose of 50 to 1600 mg (0.125 to four times the recommended dose) and multiple doses up to 2400 mg per day (three times the recommended daily dose). Maribavir PK is time-independent. With twice-daily dosing, steady state is reached within 2 days, with mean accumulation ratios of Cmax and AUC ranging from 1.37 to 1.47.

The pharmacokinetic properties of maribavir following administration of LIVTENCITY are displayed in Table 5. The multiple-dose pharmacokinetic parameters are provided in Table 6.

Table 5: Pharmacokinetic Properties of Maribavir
Absorption [When taken orally with a high fat, high caloric meal vs fasted, the AUC0‑∞ and Cmax (geometric mean ratio [90% CI] of maribavir are 0.878 [0.843, 0.915] and 0.716 [0.671, 0.764], respectively.]
Tmax (h), median | 1.0 to 3.0
Distribution
Mean apparent steady-state volume of distribution (Vss, L) | 24.9
% bound to human plasma proteins | 98.0 across the concentration range of 0.05-200 µg/mL
Blood-to plasma ratio | 1.37
Elimination
Major route of elimination | Hepatic metabolism
Half-life (t1/2) in transplant patients (h), mean | 4.32
Oral clearance (CL/F) in transplant patients (L/h), mean | 2.67
Metabolism
Metabolic pathways [In vitro studies have shown that maribavir is biotransformed into a major circulating inactive metabolite: VP 44469 (N-dealkylated metabolite), with a metabolic ratio of 0.15 - 0.20. Multiple UGT enzymes, namely UGT1A1, UGT1A3, UGT2B7, and possibly UGT1A9, are involved in the glucuronidation of maribavir in humans, however, the contribution of glucuronidation to the overall clearance of maribavir is low based on In vitro data.] | CYP3A4 (major) and CYP1A2 (minor)
Excretion
% of dose excreted as total ^14C (unchanged drug) in urine [Dosing in mass balance study: single-dose administration of [^14C] maribavir oral solution 400 mg containing 200 nCi of total radioactivity.] | 61 (<2)
% of dose excreted as total ^14C (unchanged drug) in feces | 14 (5.7)

Table 6: Multiple-Dose Pharmacokinetic Parameters of Maribavir
Geometric Mean (% CV) [Pharmacokinetic parameter values based on post-hoc estimates from maribavir population pharmacokinetic model in transplant patients with CMV receiving 400 mg of LIVTENCITY twice daily with or without food.]
AUC0-tau [tau is maribavir dosing interval: 12 hours.] (µg∙h/mL) | Cmax (µg/mL) | Ctau (µg/mL)
142 (48.5%) | 20.1 (35.5%) | 5.43 (85.9%)
CV=Coefficient of Variation; Cmax=Maximum concentration; AUC0-tau=Area under the time concentration curve over a dosing interval; Ctau=Concentration at the end of a dosing interval.

Specific Populations

There were no clinically significant differences in the pharmacokinetics of maribavir based on age (18-79 years), gender, race (Caucasian, Black, Asian, or others), ethnicity (Hispanic/Latino or non-Hispanic/Latino), body weight (36 to 141 kg), transplant type, mild to severe renal impairment (measured creatinine clearance ranging from 12 to 70 mL/min), or mild to moderate hepatic impairment (Child-Pugh Class A or B).

Pediatric Patients

The pharmacokinetics of maribavir in patients less than 18 years of age have not been evaluated.

Using modeling and simulation, the recommended dosing regimen is expected to result in comparable steady-state plasma exposures of maribavir in patients 12 years of age and older and weighing at least 35 kg as observed in adults [see Use in Specific Populations (8.4)].

Drug Interactions

Based on in vitro studies, the metabolism of maribavir is not mediated by CYP2B6, CYP2C8, CYP2C9, CYP2C19, CYP3A5, UGT1A4, UGT1A6, UGT1A10, or UGT2B15. The transport of maribavir is not mediated by organic anion transporting polypeptide (OATP)1B1, OATP1B3, or bile salt export pump (BSEP).

At clinically relevant concentrations, clinically significant interactions are not expected when LIVTENCITY is coadministered with substrates of CYP1A2, CYP2A6, CYP2B6, CYP2C8, CYP2C9, CYP2C19, CYP2E1, CYP2D6, CYP3A4; uridine diphosphate-glucuronosyltransferase (UGT)1A1, UGT1A4, UGT1A6, UGT1A9, UGT2B7; P-gp; BSEP; multidrug and toxin extrusion protein (MATE)1/2K; organic anion transporters (OAT)1 and OAT3; organic cation transporters (OCT)1 and OCT2; OATP1B1 and OATP1B3. In a clinical drug-drug interaction cocktail study, coadministration with maribavir had no effect on substrates of CYP1A2, CYP2C9, CYP2C19, CYP2D6, and CYP3A4.

Drug interaction studies were performed with LIVTENCITY and other drugs likely to be coadministered for pharmacokinetic interactions. The effects of coadministration of other drugs on the pharmacokinetics of maribavir are summarized in Table 7, and the effects of maribavir on the pharmacokinetics of coadministered drugs are summarized in Table 8.

Dosing recommendations as a result of established and other potentially significant drug-drug interactions with LIVTENCITY are provided in Table 4 [see Drug Interactions (7.3)].

Table 7: Changes in Pharmacokinetics of LIVTENCITY in the Presence of Coadministered Drugs
Coadministered Drug and Regimen |  | LIVTENCITY Regimen | N | Geometric Mean Ratio (90% CI) of LIVTENCITY PK with/without Coadministered Drug [No Effect=1.00]
Coadministered Drug and Regimen |  | LIVTENCITY Regimen | N | AUC | Cmax | Ctau [tau is maribavir dosing interval: 12 hours.]
Anticonvulsants
Carbamazepine [Based on physiologically based pharmacokinetic modeling results from 10 trials of 20 subjects each. The maribavir dosing regimen and geometric mean ratios (5th percentile, 95th percentile) correspond to dose-adjusted maribavir with inducer vs 400 mg twice daily without inducer.] | 400 mg once daily | 800 mg twice daily / 400 mg twice daily | 200 | 1.40 (1.09, 1.67) | 1.53 (1.22, 1.79) | 1.05 (0.71, 1.40)
Phenobarbital | 100 mg once daily | 1,200 mg twice daily / 400 mg twice daily | 200 | 1.80 (1.18, 2.35) | 2.17 (1.69, 2.57) | 0.94 (0.22, 1.97)
Phenytoin | 300 mg once daily | 1,200 mg twice daily / 400 mg twice daily | 200 | 1.70 (1.06, 2.46) | 2.05 (1.49, 2.63) | 0.89 (0.26, 2.04)
Antimycobacterials
Rifabutin | 300 mg once daily | 800 mg twice daily / 400 mg twice daily | 200 | 1.38 (1.00, 1.74) | 1.52 (1.17, 1.83) | 1.06 (0.64, 1.49)
Rifampin | 600 mg once daily | 400 mg twice daily | 14 | 0.40 (0.36, 0.44) | 0.61 (0.52, 0.72) | 0.18 (0.14, 0.25)
Antifungals
Ketoconazole | 400 mg single dose | 400 mg single dose | 19 | 1.53 (1.44, 1.63) | 1.10 (1.01, 1.19) | -
Antacids
Aluminum hydroxide and magnesium hydroxide antacid | 20 mL [Containing 800 mg aluminum hydroxide and 800 mg magnesium hydroxide.] single dose | 100 mg single dose | 15 | 0.89 (0.83, 0.96) | 0.84 (0.75, 0.94) | -

Table 8: Drug Interactions: Changes in Pharmacokinetics for Coadministered Drug in the Presence of 400 mg Twice Daily LIVTENCITY
Coadministered Drug and Regimen |  | N | Geometric Mean Ratio (90% CI) of Coadministered Drug PK with/without LIVTENCITY [No Effect=1.00]
Coadministered Drug and Regimen |  | N | AUC | Cmax | Ctau
Immunosuppressants
Tacrolimus | stable dose, twice daily (total daily dose: 0.5-16 mg) | 20 | 1.51 (1.39, 1.65) | 1.38 (1.20, 1.57) | 1.57 (1.41, 1.74)
P-gp substrate
Digoxin | 0.5 mg single dose | 18 | 1.21 (1.10, 1.32) | 1.25 (1.13, 1.38) | -

12.4 Microbiology

Mechanism of Action

The antiviral activity of maribavir is mediated by competitive inhibition of the protein kinase activity of human CMV enzyme pUL97, which results in inhibition of the phosphorylation of proteins. Maribavir inhibited wild-type pUL97 protein kinase in a biochemical assay with an IC50 value of 0.003 µM. Maribavir and its 5'-mono- and 5'-triphosphate derivatives at 100 µM had no significant effect on the incorporation of deoxynucleoside triphosphates by human CMV DNA polymerase. At a concentration of 100 µM, neither maribavir nor its 5′-triphosphate derivative inhibited CMV DNA polymerase delta, however the 5′-monophosphate derivative inhibited incorporation by polymerase delta of all 4 natural dNTPs by approximately 55%.

Antiviral Activity

Maribavir inhibited human CMV replication in virus yield reduction, DNA hybridization, and plaque reduction assays in human lung fibroblast cell line (MRC-5), human embryonic kidney (HEK), and human foreskin fibroblast (MRHF) cells. The EC50 values ranged from 0.03 to 2.2 µM depending on the cell line and assay endpoint. The cell culture antiviral activity of maribavir has also been evaluated against CMV clinical isolates. The median EC50 values were 0.1 µM (n=10, range 0.03-0.13 µM) and 0.28 µM (n=10, range 0.12-0.56 µM) using DNA hybridization and plaque reduction assays, respectively. No significant difference in EC50 values across the four human CMV glycoprotein B genotypes (N=2, 1, 4, and 1 for gB1, gB2, gB3, and gB4, respectively) was seen.

Combination Antiviral Activity

When maribavir was tested in combination with other antiviral compounds, antagonism of the antiviral activity was seen in combination with ganciclovir. No antagonism was observed with cidofovir, foscarnet, letermovir and rapamycin at the drugs EC50 values. The pUL97 kinase activity inhibited by maribavir is necessary to activate valganciclovir/ganciclovir.

Treatment Effect in CMV Glycoprotein B (gB) Subtypes

In Trial 303, the primary endpoint response rates for LIVTENCITY across CMV gB subtypes 1, 2, 3, 4, and 5 were 65% (55/85), 39% (22/57), 54% (22/41), 67% (14/21), and 64% (7/11), respectively. The primary endpoint response rates for IAT across CMV gB subtypes 1, 2, 3, 4, and 5 were 28% (15/53), 27% (4/15), 11% (2/19), 20% (2/10), and 17% (1/6), respectively [see Clinical Studies (14)].

Viral Resistance

In Cell Culture

Selection of maribavir resistant virus in cell culture and genotypic plus phenotypic characterization of these has identified amino acid substitutions that confer reduced susceptibility to maribavir. Substitutions identified in pUL97 include L337M, V353A, L397R, T409M, and H411L/N/Y. These substitutions confer reductions in susceptibility that range from 3.5-fold to >200-fold. Substitutions were also identified in pUL27:R233S, W362R, W153R, L193F, A269T, V353E, L426F, E22stop, W362stop, 218delC, and 301-311del. These substitutions confer reductions in susceptibility that range from 1.7- to 4.8-fold.

In Clinical Studies

In Phase 2 Study 202 evaluating maribavir in 120 hematopoietic stem cell transplant (HSCT) or solid organ transplant (SOT) recipients with phenotypic resistance to valganciclovir/ganciclovir, DNA sequence analysis of a select region of pUL97 (amino acids 270 to 482) and pUL27 (amino acids 108 to 424) was performed on 34 paired virologic failure samples. There were 25 patients with treatment-emergent maribavir resistance-associated substitution(s) in pUL97 F342Y (4.5-fold reduction in susceptibility), T409M (78-fold reduction), H411L/Y (69- and 12-fold reduction) and/or C480F (224-fold reduction).

In Phase 3 Study 303 evaluating maribavir in patients with phenotypic resistance to valganciclovir/ganciclovir, DNA sequence analysis of the entire coding regions of pUL97 and pUL27 was performed on 134 paired sequences from maribavir-treated patients. The treatment-emergent pUL97 substitutions F342Y (4.5-fold), T409M (78-fold), H411L/N/Y (69-, 9-, and 12-fold, respectively), and/or C480F (224-fold) were detected in 58 subjects (47 subjects were on-treatment failures and 11 subjects were relapsers). One subject with the pUL27 L193F substitution (2.6-fold reduced susceptibility to maribavir) at baseline did not meet the primary endpoint.

Cross-Resistance

Cross-resistance has been observed between maribavir and ganciclovir/valganciclovir in cell culture and in clinical studies.

pUL97 valganciclovir/ganciclovir resistance-associated substitutions F342S/Y, K355del, V356G, D456N, V466G, C480R, P521L, and Y617del reduce susceptibility to maribavir >4.5-fold. Other vGCV/GCV resistance pathways have not been evaluated for cross-resistance to maribavir. pUL54 DNA polymerase substitutions conferring resistance to vGCV/GCV, cidofovir, or foscarnet remained susceptible to maribavir.

Substitutions pUL97 F342Y and C480F are maribavir treatment-emergent resistance-associated substitutions that confer >1.5-fold reduced susceptibility to vGCV/GCV, a fold reduction that is associated with phenotypic resistance to vGCV/GCV. The clinical significance of this cross-resistance to vGCV/GCV for these substitutions has not been determined. Maribavir resistant virus remained susceptible to cidofovir and foscarnet. Additionally, there are no reports of any pUL27 maribavir resistance-associated substitutions being evaluated for vGCV/GCV, cidofovir, or foscarnet cross-resistance. Given the lack of resistance-associated substitutions for these drugs mapping to pUL27, cross-resistance is not expected for pUL27 maribavir substitutions.

13 NONCLINICAL TOXICOLOGY

13.1 Carcinogenesis, Mutagenesis, Impairment of Fertility

Two-year carcinogenicity studies were conducted in mice and rats administered oral doses up to 150 and 100 mg/kg/day, respectively. Maribavir was not carcinogenic in rats at any dose tested, corresponding to maribavir exposures less than human exposure at the RHD. At 150 mg/kg/day in male mice only, an increased incidence of hemangioma, hemangiosarcoma, and combined hemangioma/hemangiosarcoma was observed across multiple tissues, at exposures less than the human exposure at the RHD. There were no carcinogenic findings in male mice at ≤75 mg/kg/day and female mice at any dose.

Mutagenicity

Maribavir was negative in a bacterial mutation assay and the in vivo rat bone marrow micronucleus assay. Maribavir was positive in the absence of metabolic activation in the mouse lymphoma assay, and the results were equivocal in the presence of metabolic activation.

Impairment of Fertility

Although decreased sperm straight line velocity was observed in males (at maribavir exposures less than those observed in humans at the RHD), there were no effects on fertility in males or females in a combined oral fertility and embryo-fetal study in rats administered maribavir at up to 400 mg/kg/day [see Use in Specific Populations (8.1)].

14 CLINICAL STUDIES

14.1 Treatment of Adults with Post-Transplant CMV Infection/Disease That Is Refractory (with or without Genotypic Resistance) to Ganciclovir, Valganciclovir, Cidofovir, or Foscarnet

LIVTENCITY was evaluated in a Phase 3, multicenter, randomized, open-label, active-controlled superiority trial (NCT02931539, Trial 303) to assess the efficacy and safety of LIVTENCITY compared to Investigator-Assigned Treatment (IAT) (ganciclovir, valganciclovir, foscarnet, or cidofovir) in 352 HSCT or SOT recipients with CMV infections that were refractory to treatment with ganciclovir, valganciclovir, foscarnet, or cidofovir, including CMV infections with or without confirmed resistance to 1 or more of the IATs. Subjects with CMV disease involving the central nervous system, including the retina, were excluded from the study.

Subjects were stratified by transplant type (HSCT or SOT) and screening CMV DNA levels and then randomized in a 2:1 allocation ratio to receive either LIVTENCITY 400 mg twice daily or IAT as dosed by the investigator for up to 8 weeks. After completion of the treatment period, subjects entered a 12-week follow-up phase.

The mean age of trial subjects was 53 years and most subjects were male (61%), white (76%) and not Hispanic or Latino (83%), with similar distributions across the two treatment arms. The most common treatment used in the IAT arm was foscarnet which was administered in 47 (41%) subjects followed by ganciclovir or valganciclovir, each administered in 28 (24%) subjects. Cidofovir was administered in 6 subjects, the combination of foscarnet and valganciclovir in 4 subjects and the combination of foscarnet and ganciclovir in 3 subjects. Baseline disease characteristics are summarized in Table 9 below.

Table 9: Summary of Baseline Disease Characteristics in Trial 303
Characteristic | LIVTENCITY 400 mg Twice Daily N=235 n (%) | IAT N=117 n (%)
Characteristic | Transplant type
HSCT | 93 (40) | 48 (41)
SOT | 142 (60) | 69 (59)
Kidney | 74 (52) | 32 (46)
Lung | 40 (28) | 22 (32)
Heart | 14 (10) | 9 (13)
Other (multiple, liver, pancreas, intestine) | 14 (10) | 6 (9)
CMV DNA levels
Low (<9,100 IU/mL) | 153 (65) | 85 (73)
Intermediate (≥9,100 to <91,000 IU/mL) | 68 (29) | 25 (21)
High (≥91,000 IU/mL) | 14 (6) | 7 (6)
Confirmed symptomatic CMV infection at baseline
No | 214 (91) | 109 (93)
Yes [one of the subjects had both CMV syndrome and disease but was counted for CMV disease only.] | 21 (9) | 8 (7)
CMV syndrome (SOT only) | 9 (43) | 7 (88)
Tissue Invasive disease | 12 (57) | 1 (13)
CMV=cytomegalovirus, DNA=deoxyribonucleic acid, HSCT=hematopoietic stem cell transplant, IAT=investigator assigned anti-CMV treatment, N=number of patients, SOT=solid organ transplant.

Primary Efficacy Endpoint

The primary efficacy endpoint was confirmed CMV DNA level < LLOQ (i.e., <137 IU/mL) as assessed by COBAS® AmpliPrep/COBAS® TaqMan® CMV test) at the end of Week 8. The key secondary endpoint was CMV DNA level < LLOQ and CMV infection symptom control at the end of Study Week 8 with maintenance of this treatment effect through Study Week 16.

For the primary endpoint, LIVTENCITY was statistically superior to IAT (56% vs 24%, respectively), as shown in Table 10.

Table 10: Primary Efficacy Endpoint Analysis at Week 8 (Randomized Set) in Trial 303
 | LIVTENCITY 400 mg Twice Daily N=235 n (%) | IAT N=117 n (%)
Primary Endpoint: Confirmed CMV DNA Level < LLOQ at Week 8 [Confirmed CMV DNA level < LLOQ at the end of Week 8 (2 consecutive samples separated by at least 5 days with DNA levels < LLOQ [i.e.:, <137 IU/mL]).]
Responders | 131 (56) | 28 (24)
Adjusted difference in proportion of responders (95% CI) [Cochran-Mantel-Haenszel weighted average approach was used for the adjusted difference in proportion (maribavir – IAT), the corresponding 95% CI, and the p-value after adjusting for the transplant type and baseline plasma CMV DNA concentration. Only those with both stratification factors were included in the computation.] | 33 (23, 43)
p-value: adjusted | <0.001
CI=confidence interval; CMV=cytomegalovirus; IAT=investigator-assigned anti-CMV treatment; N=number of patients.

The reasons for failure to meet the primary endpoint are summarized in Table 11.

Table 11: Analysis of Failures for Primary Efficacy Endpoint
Outcome at Week 8 | LIVTENCITY N=235 n (%) | IAT N=117 n (%)
Responders (Confirmed DNA Level < LLOQ) [Confirmed CMV DNA level < LLOQ at the end of Week 8 (2 consecutive samples separated by at least 5 days with DNA levels < LLOQ [i.e.:, <137 IU/mL]).] | 131 (56) | 28 (24)
Non-responders: | 104 (44) | 89 (76)
Due to virologic failure [CMV DNA breakthrough=achieved confirmed CMV DNA level < LLOQ and subsequently became detectable.] : | 80 (34) | 42 (36)
• CMV DNA never < LLOQ | 48 (20) | 35 (30)
• CMV DNA breakthrough | 32 (14) | 7 (6)
Due to drug/study discontinuation: | 21 (9) | 44 (38)
• Adverse events | 8 (3) | 26 (22)
• Deaths | 10 (4) | 3 (3)
• Withdrawal of consent | 1 (<1) | 9 (8)
• Other reasons [Other reasons=other reasons not including adverse events, deaths and lack of efficacy, withdrawal of consent, and non-compliance.] | 2 (1) | 6 (5)
Due to other reasons but remained on study [Includes subjects who completed study assigned treatment and were non-responders.] | 3 (1) | 3 (3)
CMV=Cytomegalovirus, IAT=Investigator-assigned anti-CMV Treatment, MBV=maribavir.
Percentages are based on the number of subjects in the Randomized Set.

The treatment effect of LIVTENCITY was consistent across transplant type, age group, and the presence of CMV syndrome/disease at baseline. However, LIVTENCITY was less effective against subjects with increased CMV DNA levels (≥50,000 IU/mL) and subjects with absence of genotypic resistance (see Table 12).

Table 12: Responders by Subgroup in Trial 303
 | LIVTENCITY 400 mg Twice Daily N=235 |  | IAT N=117
 | n/N | % | n/N | %
Transplant type
SOT | 79/142 | 56 | 18/69 | 26
HSCT | 52/93 | 56 | 10/48 | 21
Baseline CMV DNA viral load
Low (<9,100 IU/mL) | 95/153 | 62 | 21/85 | 25
Intermediate (≥9,100 to <91,000 IU/mL) | 32/68 | 47 | 5/25 | 20
≥9,100 to <50,000 IU/mL | 29/59 | 49 | 4/20 | 20
≥50,000 to <91,000 IU/mL | 3/9 | 33 | 1/5 | 20
High (≥91,000 IU/mL) | 4/14 | 29 | 2/7 | 29
Genotypic resistance to other anti-CMV agents
Yes | 76/121 | 63 | 15/70 | 21
No | 42/96 | 44 | 10/33 | 30
CMV syndrome/disease at baseline
Yes | 10/21 | 48 | 1/8 | 13
No | 121/214 | 57 | 27/109 | 25
Age Group
18 to 44 years | 28/55 | 51 | 8/32 | 25
45 to 64 years | 71/126 | 56 | 19/69 | 28
≥65 years | 32/54 | 59 | 1/16 | 6

Secondary Endpoints

Table 13 shows results of the secondary endpoint, achievement of CMV DNA level < LLOQ and symptom controla at Week 8 with maintenance through Week 16.

Table 13: Achievement of CMV DNA Level < LLOQ and CMV Infection Symptom Control at Week 8, With Maintenance Through Week 16 [CMV infection symptom control was defined as resolution or improvement of tissue-invasive disease or CMV syndrome for symptomatic patients at baseline, or no new symptoms for patients who were asymptomatic at baseline.]
 | LIVTENCITY 400 mg Twice Daily N=235 n (%) | IAT N=117 n (%)
Responders | 44 (19) | 12 (10)
Adjusted difference in proportion of responders (95% CI) [Cochran-Mantel-Haenszel weighted average approach was used for the adjusted difference in proportion (maribavir – IAT), the corresponding 95% CI, and the p-value after adjusting for the transplant type and baseline plasma CMV DNA concentration. Only those with both stratification factors were included in the computation.] | 9 (2,17)
p-value: adjusted | 0.013

Virologic relapse during follow-up period: After the end of treatment phase, 65/131 (50%) of subjects in the LIVTENCITY group and 11/28 (39%) subjects in the IAT group who achieved CMV DNA level < LLOQ experienced virologic relapse during the follow-up period. Most of the relapses 58/65 (89%) in LIVTENCITY group and 11/11 (100% in IAT group)] occurred within 4 weeks after study drug discontinuation; and the median time to relapse after CMV DNA level < LLOQ was 15 days (range 7, 71) in the LIVTENCITY group and 15 days (range 7, 29) in the IAT group [see Warnings and Precautions (5.2) and Microbiology (12.4)].

New onset symptomatic CMV infection: For the entire study period, a similar percentage of subjects in each treatment group developed new onset symptomatic CMV infection (LIVTENCITY 6% [14/235]; IAT 6% [7/113]).

Overall mortality: All-cause mortality was assessed for the entire study period. A similar percentage of subjects in each treatment group died during the trial (LIVTENCITY 11% [27/235]; IAT 11% [13/117]).

16 HOW SUPPLIED/STORAGE AND HANDLING

Tablet: 200 mg, blue, oval shaped convex tablet debossed with "SHP" on one side and "620" on the other side. They are supplied as follows:

Bottles of 28 tablets with child-resistant caps (NDC 64764-800-28)

Bottles of 56 tablets with child-resistant caps (NDC 64764-800-56)

Storage and Handling

Store at 20°C to 25°C (68°F to 77°F), brief exposure to 15°C to 30°C (59°F to 86°F) permitted [see USP Controlled Room Temperature].

17 PATIENT COUNSELING INFORMATION

Advise the patient to read the FDA-approved patient labeling (Patient Information and Instructions for Use).

Inform patients that LIVTENCITY may interact with other drugs. Advise patients to report to their healthcare provider the use of any other medication [see Warnings and Precautions (5.1 and 5.3), Drug Interactions (7)].

Distributed by:
Takeda Pharmaceuticals America, Inc.
Cambridge, MA 02142

LIVTENCITY and are registered trademarks of Takeda Pharmaceuticals International AG.

TAKEDA and are registered trademarks of Takeda Pharmaceutical Company Limited.

©2025 Takeda Pharmaceuticals U.S.A., Inc. All rights reserved.

MAR358 R5

Patient Information
LIVTENCITY (liv-TEN-city)
(maribavir)
tablets

What is LIVTENCITY?

LIVTENCITY is a prescription medicine used to treat cytomegalovirus (CMV) infection and disease in adults and children 12 years of age and older weighing at least 77 pounds (35 kg) who have received a transplant, when their infection or disease does not respond to treatment with the medicines ganciclovir, valganciclovir, cidofovir or foscarnet.

It is not known if LIVTENCITY is safe and effective in children under 12 years of age.

Before taking LIVTENCITY, tell your healthcare provider about all your medical conditions, including if you:

- are pregnant or plan to become pregnant. It is not known if LIVTENCITY will harm your unborn baby.
- are breastfeeding or plan to breastfeed. It is not known if LIVTENCITY passes into your breast milk. Talk to your healthcare provider about the best way to feed your baby during treatment with LIVTENCITY.

Tell your healthcare provider about all of the medicines you take, including prescription and over-the-counter medicines, vitamins and herbal supplements. LIVTENCITY may affect the way other medicines work, and other medicines may affect how LIVTENCITY works and cause serious side effects.

Especially tell your healthcare provider if you take a seizure (anticonvulsant) medicine.

- You can ask your healthcare provider or pharmacist for a list of medicines that interact with LIVTENCITY.
- Do not start a new medicine without telling your healthcare provider. Your healthcare provider will tell you if it is safe to take LIVTENCITY with other medicines.
- Know the medicines you take. Keep a list of your medicines and show it to your healthcare provider and pharmacist when you get a new medicine.

How should I take LIVTENCITY?

- Take LIVTENCITY exactly as your healthcare provider tells you to take it.
- Take LIVTENCITY 2 times a day.
- Take LIVTENCITY with or without food.
- Swallow LIVTENCITY tablets whole.
- If you are not able to swallow tablets whole, you can break apart (disperse) the tablets in drinking water or crush the tablets and mix with drinking water and take by mouth. See the "Instructions for Use" for detailed instructions on how to prepare and give a dose of LIVTENCITY tablets by dispersing or crushing tablets and taking by mouth.
- If you have a Nasogastric (NG) or Orogastric (OG) Tube (French size 10 or larger), you can disperse the tablets and take through a NG or OG tube. See the "Instructions for Use" for detailed instructions on how to prepare and give a dose of LIVTENCITY tablets through a NG or OG Tube.
- If you take too much LIVTENCITY, call your healthcare provider or go to the nearest hospital emergency room right away.

What are the possible side effects of LIVTENCITY?

The most common side effects of LIVTENCITY include:

- changes in taste
- nausea
- diarrhea

- vomiting
- tiredness

These are not all the possible side effects of LIVTENCITY.

Call your doctor for medical advice about side effects. You may report side effects to FDA at 1-800-FDA-1088.

How should I store LIVTENCITY?

- Store LIVTENCITY at room temperature between 68°F to 77°F (20°C to 25°C).

Keep LIVTENCITY and all medicines out of the reach of children.

General information about the safe and effective use of LIVTENCITY.

Medicines are sometimes prescribed for purposes other than those listed in the Patient Information leaflet. Do not use LIVTENCITY for a condition for which it was not prescribed. Do not give LIVTENCITY to other people, even if they have the same symptoms that you have. It may harm them. You can ask your pharmacist or healthcare provider for information about LIVTENCITY that is written for health professionals.

What are the ingredients in LIVTENCITY?

Active ingredient: maribavir

Inactive ingredients: FD&C Blue #1, magnesium stearate, microcrystalline cellulose, polyethylene glycol, polyvinyl alcohol, sodium starch glycolate, titanium dioxide, and talc.

Distributed by: Takeda Pharmaceuticals America, Inc., Cambridge, MA 02142

LIVTENCITY and are registered trademarks of Takeda Pharmaceuticals International AG.

TAKEDA and are registered trademarks of Takeda Pharmaceutical Company Limited.

©2024 Takeda Pharmaceuticals U.S.A., Inc. All rights reserved.
For more information, go to www.explorelivtencity.com or call 1-877-TAKEDA-7 (1-877-825-3327).

This Patient Information has been approved by the U.S. Food and Drug Administration. MAR358 R4

Revised: March 2024

Instructions for Use

LIVTENCITY (liv-TEN-city)
(maribavir)
tablets, for oral use

This Instructions for Use contains information on how to prepare and give a dose of LIVTENCITY tablets by breaking apart (dispersing) or crushing in drinking water and taking by mouth; or dispersing and giving through a Nasogastric (NG) or Orogastric (OG) Tube. Read this Instructions for Use before you prepare or give the first dose of LIVTENCITY, and each time you get a refill. Ask your healthcare provider or pharmacist if you have any questions.

Important information you need to know before preparing a dose of LIVTENCITY:

- You can break apart (disperse) the tablets in drinking water or crush the tablets and mix with drinking water. The tablet will not be completely dispersed in the mixture.
- Do not mix LIVTENCITY with any liquid other than drinking water.
- LIVTENCITY tablets that have been dispersed in drinking water can be given through a Nasogastric (NG) or Orogastric (OG) tube (French size 10 or larger).
- You can prepare the mixture ahead of time and store at room temperature 68°F to 77°F (20°C to 25°C) for up to 8 hours.

Preparing a dose of LIVTENCITY by dispersing or crushing tablets and taking by mouth:

Gather the following supplies:

- small, clean container to place tablets and water in
- drinking water

Step 1: Choose a clean, flat work surface. Place all supplies on the work surface.

Step 2: Wash and dry your hands well.

Step 3: Get the prescribed number of LIVTENCITY tablets needed to prepare the dose.

Step 4: Place the LIVTENCITY tablets into the container.

Note: If you prefer, you can crush the tablets with a spoon before adding water.

Step 5: Add the amount of drinking water needed for your prescribed dose.

Number of Tablets | Amount of Drinking Water
2 | 30 mL
4 | 60 mL
6 | 90 mL

Step 6: Swirl the container gently to disperse the tablets in the water and swallow the mixture right away. The mixture will have a bitter taste.

Step 7: Rinse the container with 15 mL of drinking water and swallow the mixture.

Repeat Step 7. Check that no pieces of tablet are left in the container. Repeat Step 7 until no pieces remain.

Preparing and giving a dose of LIVTENCITY through a Nasogastric (NG) or Orogastric (OG) Tube:

Gather the following supplies:

- 50 mL or 60 mL syringe
- drinking water

Step 1: Remove the cap (if capped) and plunger out of a 50 mL or 60 mL syringe. Add 2 tablets into the syringe body and place the plunger back in the syringe.

Note: Only 2 tablets can be given through the NG or OG tube at a time.

Step 2: Withdraw 30 mL of drinking water into the syringe.

Step 3: Hold the syringe with the tip pointing upward. Pull the plunger back so there is some air space in the syringe. If there is a cap, place the cap back on the syringe. Shake the syringe well for about 30 to 45 seconds or until the tablets are completely dispersed. Be careful not to spill the contents of the syringe.

Step 4: Remove the cap (if capped) from the syringe again and attach the syringe to the NG or OG tube and give the mixture right away.

Step 5: Withdraw 15 mL of drinking water into the same syringe and flush through the NG or OG tube.

Repeat Step 5. Check that no pieces of tablet are left in the syringe. Repeat Step 5 until no pieces remain.

Note: If your prescribed dose is more than 2 tablets, Repeat Steps 1 through 5 until you give the full prescribed dose.

Storing LIVTENCITY:

- Store LIVTENCITY at room temperature 68°F to 77°F (20°C to 25°C).

Keep LIVTENCITY and all medicines out of the reach of children.

For more information, go to www.explorelivtencity.com or call 1-877-TAKEDA-7 (1-877-825-3327).

Distributed by: Takeda Pharmaceuticals America, Inc., Cambridge, MA 02142

LIVTENCITY and are registered trademarks of Takeda Pharmaceuticals International AG.
TAKEDA and are registered trademarks of Takeda Pharmaceutical Company Limited.
©2024 Takeda Pharmaceuticals U.S.A., Inc. All rights reserved.

This Instructions for Use has been approved by the U.S. Food and Drug Administration.
MAR358 R4
Revised: March 2024

PRINCIPAL DISPLAY PANEL - 200 mg Bottle Carton

NDC 64764-800-28

LIVTENCITY®
(maribavir) tablets
200 mg

Rx Only
28 Tablets

For Oral Use

Takeda

PRINCIPAL DISPLAY PANEL - 200 mg Bottle Carton

NDC 64764-800-56

LIVTENCITY®
(maribavir) tablets
200 mg

Rx Only
56 Tablets

For Oral Use

Takeda